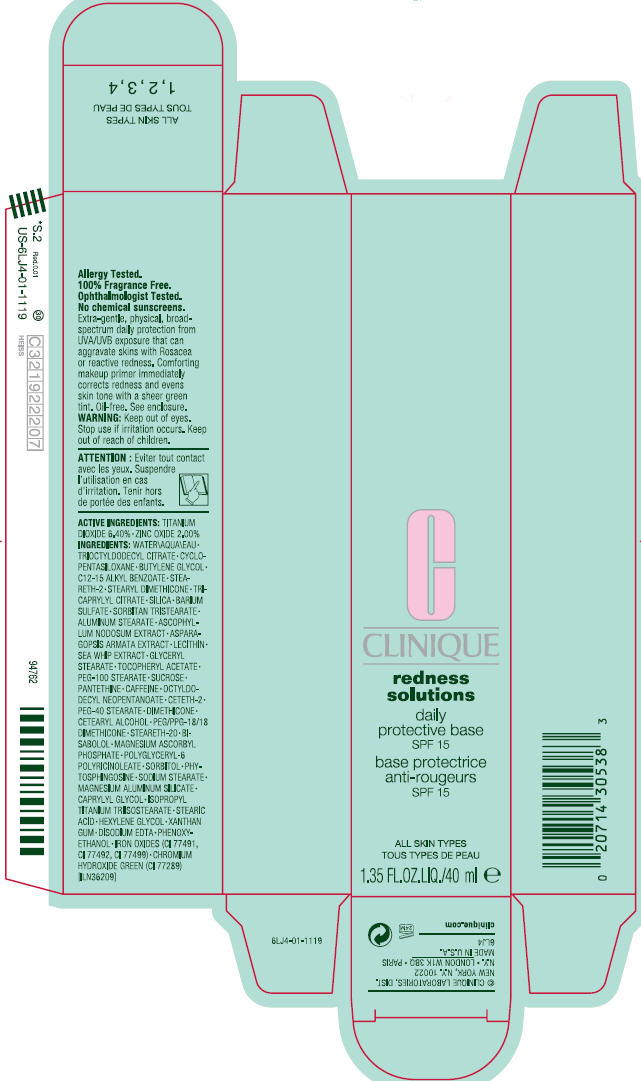 DRUG LABEL: CLINIQUE REDNESS SOLUTIONS 
NDC: 49527-722 | Form: CREAM
Manufacturer: CLINIQUE LABORATORIES INC
Category: otc | Type: HUMAN OTC DRUG LABEL
Date: 20111201

ACTIVE INGREDIENTS: TITANIUM DIOXIDE 6.4 mL/100 mL; ZINC OXIDE 2 mL/100 mL
INACTIVE INGREDIENTS: water; cyclomethicone 5; butylene glycol; alkyl (c12-15) benzoate; steareth-2; tricaprylyl citrate; silicon dioxide; barium sulfate; sorbitan tristearate; aluminum stearate; ascophyllum nodosum; asparagopsis armata; pseudopterogorgia elisabethae; glyceryl monostearate; alpha-tocopherol acetate; peg-100 stearate; sucrose; pantethine; caffeine; octyldodecyl neopentanoate; ceteth-2; peg-40 stearate; dimethicone; cetostearyl alcohol; steareth-20; levomenol; magnesium ascorbyl phosphate; sorbitol; sodium stearate; magnesium aluminum silicate; caprylyl glycol; stearic acid; hexylene glycol; xanthan gum; edetate disodium; phenoxyethanol; ferric oxide red; ferric oxide yellow; ferrosoferric oxide

CLINIQUE
redness solutions

WARNING

Keep out of eyes.

Stop use if irritation occurs.

Keep out of reach of children

ACTIVE INGREDIENTS

TITANIUM DIOXIDE 6.40% • ZINC OXIDE 2.00%

INGREDIENTS

WATER • TRIOCTYLDODECYL CITRATE • CYCLOPENTASILOXANE • BUTYLENE GLYCOL • C12-15 ALKYL BENZOATE • STEARETH-2 • STEARYL DIMETHICONE • TRICAPRYLYL CITRATE • SILICA • BARIUM SULFATE • SORBITAN TRISTEARATE • ALUMINUM STEARATE • ASCOPHYLLUM NODOSUM EXTRACT • ASPARAGOPSIS ARMATA EXTRACT • LECITHIN • SEA WHIP EXTRACT • GLYCERYL STEARATE • TOCOPHERYL ACETATE • PEG-100 STEARATE • SUCROSE • PANTETHINE • CAFFEINE • OCTYLDODECYL NEOPENTANOATE • CETETH-2 • PEG-40 STEARATE • DIMETHICONE • CETEARYL ALCOHOL • PEG/PPG-18/18 DIMETHICONE • STEARETH-20 • BISABOLOL • MAGNESIUM ASCORBYL PHOSPHATE • POLYGLYCERYL-6 POLYRICINOLEATE • SORBITOL • PHYTOSPHINGOSINE • SODIUM STEARATE • MAGNESIUM ALUMINUM SILICATE • CAPRYLYL GLYCOL • ISOPROPYL TITANIUM TRIISOSTEARATE • STEARIC ACID • HEXYLENE GLYCOL • XANTHAN GUM • DISODIUM EDTA • PHENOXYETHANOL • IRON OXIDES (CI 77491, CI 77492, CI 77499) • CHROMIUM HYDROXIDE GREEN (CI 77289) [ILN36209]

© CLINIQUE LABORATORIES, DIST.
NEW YORK, N.Y. 10022

PRINCIPAL DISPLAY PANEL - 40 ml Carton

CLINIQUE

redness
solutions

daily
protective base
SPF 15

ALL SKIN TYPES

1.35 FL.OZ.LIQ./40 ml e